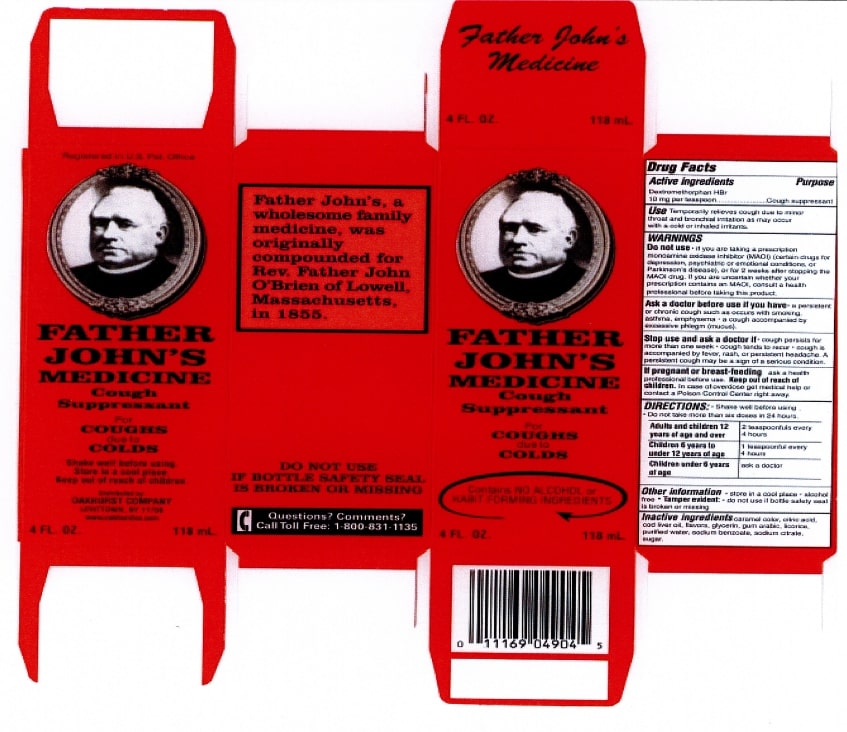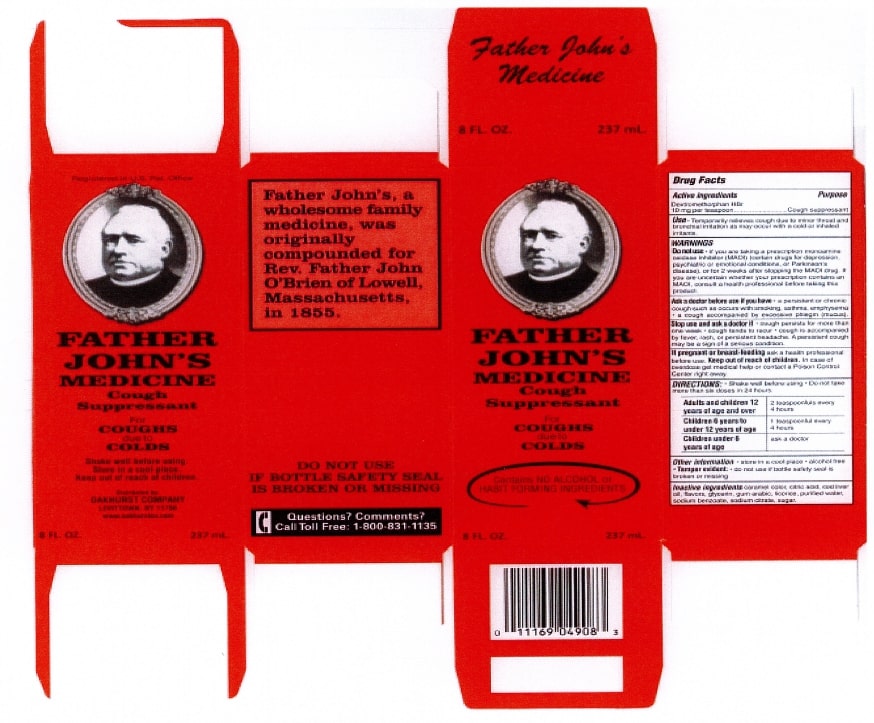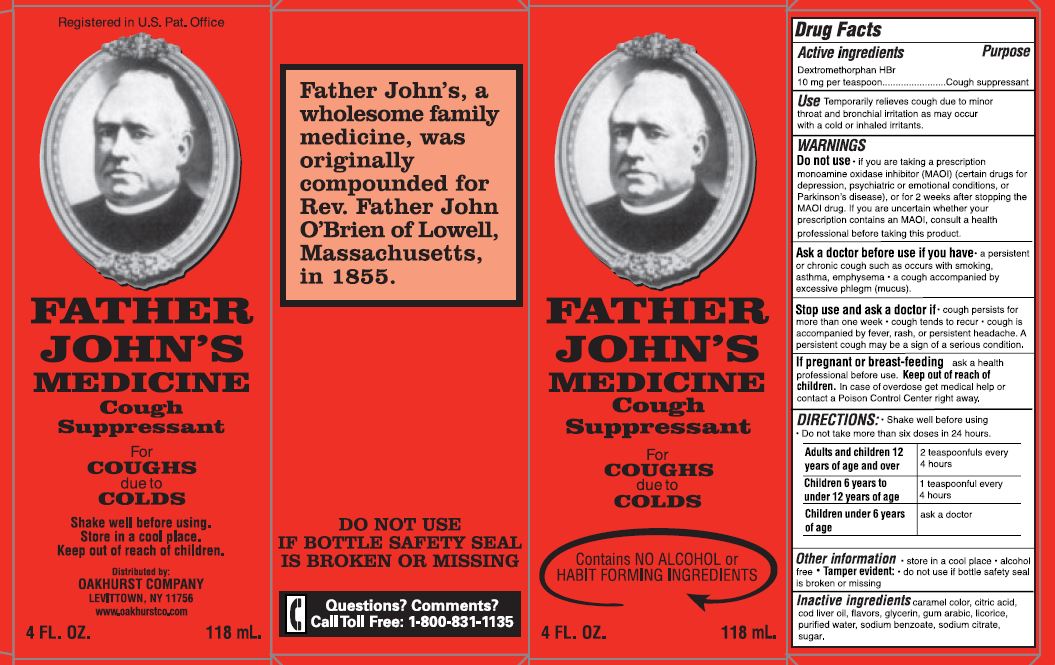 DRUG LABEL: Father Johns Medicine
NDC: 45728-444 | Form: LIQUID
Manufacturer: Oakhurst Company
Category: otc | Type: HUMAN OTC DRUG LABEL
Date: 20231218

ACTIVE INGREDIENTS: DEXTROMETHORPHAN HYDROBROMIDE 10 mg/5 mL
INACTIVE INGREDIENTS: LICORICE; CLOVE OIL; SUCROSE; LAVENDER OIL; NUTMEG OIL; CINNAMALDEHYDE; CARAMEL; GLYCERIN; COD LIVER OIL; ACACIA; WATER

Father John's Medicine

DOSAGE AND ADMINISTRATION

Shake well before using. Do not take more than six doses in 24 hours.

Adults and children 12 years of age and over | 2 teaspoons every 4 hours

Children 6 years to under 12 years of age | 1 teaspoon every 4 hours

Children under 6 years of age | ask a doctor

Do not use:

If youa re now taking a prescription monoamine oxidase inhibitor (MAOI) (Certain drugs for depression, psychiatric or emotional conditions, or parkinsons disease), or for 2 weeks after stopping the maoi drug. if you are uncertain whether your prescription contains a MAOI, consult a health professional before taking this product.

INACTIVE INGREDIENT

Carmael Color

Citric Acid

Cod liver oil

Flavors

Glycerin

Gum Arabic

Licorice

Purified Water

Sodium Benzoate

Sodium Citrate

Sugar

ACTIVE INGREDIENT

Dextrinetgirogab HBr....... 10 mg per teaspoon

INDICATIONS AND USAGE

Temporarily relieves cough due to minor throat and bronchial irritation as may occur with a cold or inhaled irritants.

PURPOSE

Cough Suppresant

Keep out of reach of children. In case of overdose get medical help or contact a poison control center right away.